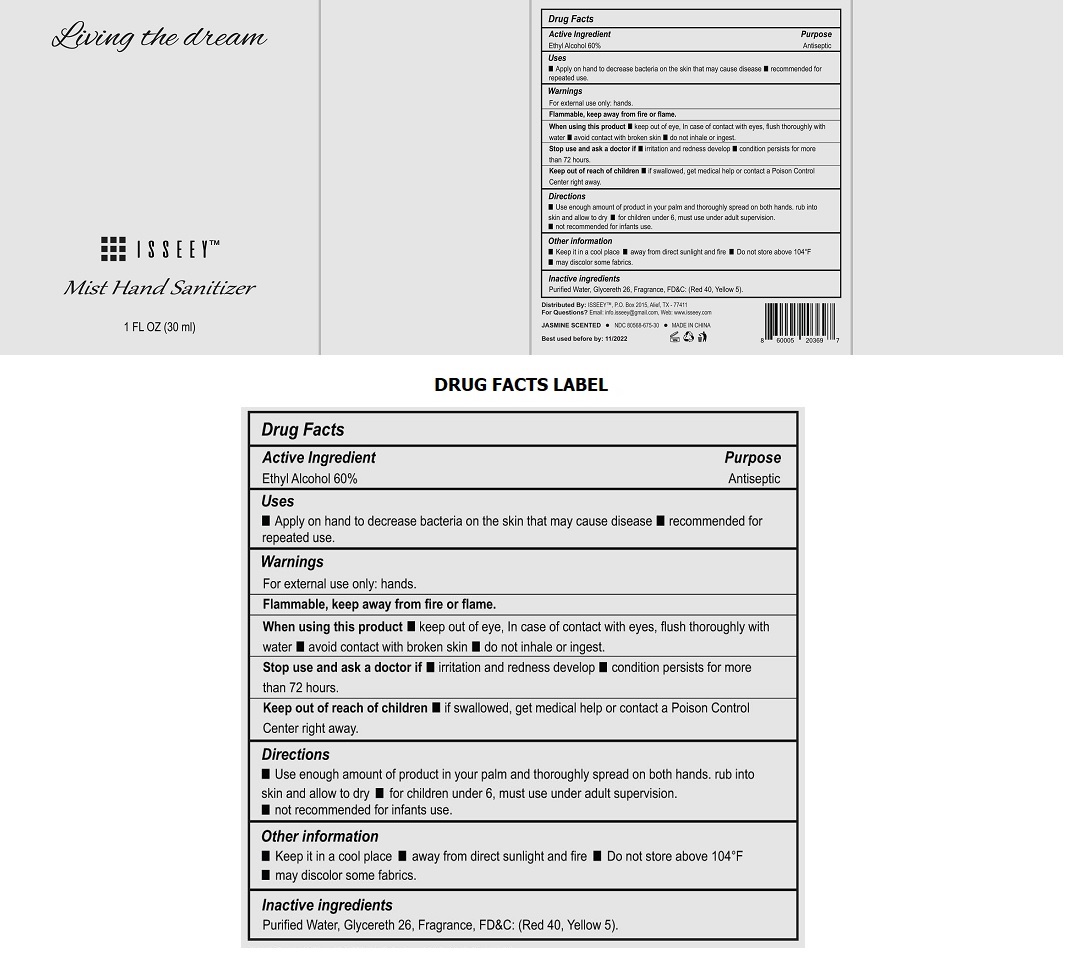 DRUG LABEL: ISSEEY - MIST HAND SANITIZER - LIVING THE DREAM
NDC: 80568-675 | Form: LIQUID
Manufacturer: ISSEEY
Category: otc | Type: HUMAN OTC DRUG LABEL
Date: 20210113

ACTIVE INGREDIENTS: ALCOHOL 60 mL/100 mL
INACTIVE INGREDIENTS: WATER; GLYCERETH-26; FD&C RED NO. 40; FD&C YELLOW NO. 5

ISSEEY™ Mist Hand Sanitizer - Living the dream

Active Ingredient

Ethyl Alcohol 60%

Purpose

Antiseptic

Uses

• Apply on hand to decrease bacteria on the skin that may cause disease • recommended for repeated use.

Warnings

For external use only: hands.

Flammable, keep away from fire or flame.

When using this product • keep out of eye, In case of contact with eyes, flush thoroughly with water • avoid contact with broken skin • do not inhale or ingest.

Stop use and ask a doctor if • irritation and redness develop • condition persists for more than 72 hours.

Keep out of reach of children • if swallowed, get medical help or contact a Poison Control Center right away.

Directions

• Use enough amount of product in your palm and thoroughly spread on both hands. rub into skin and allow to dry • for children under 6, must use under adult supervision. • not recommended for infants use.

Other information

• Keep it in a cool place • away from direct sunlight and fire • Do not store above 104°F • may discolor some fabrics.

Inactive ingredients

Purified Water, Glycereth 26, Fragrance, FD&C: (Red 40, Yellow 5).

Distributed By: ISSEEY™, P.O.Box 2015, Alief, TX - 77411
For Questions? Email: info.isseey@gmail.com, Web: www.isseey.com

JASMINE SCENTED • MADE IN CHINA